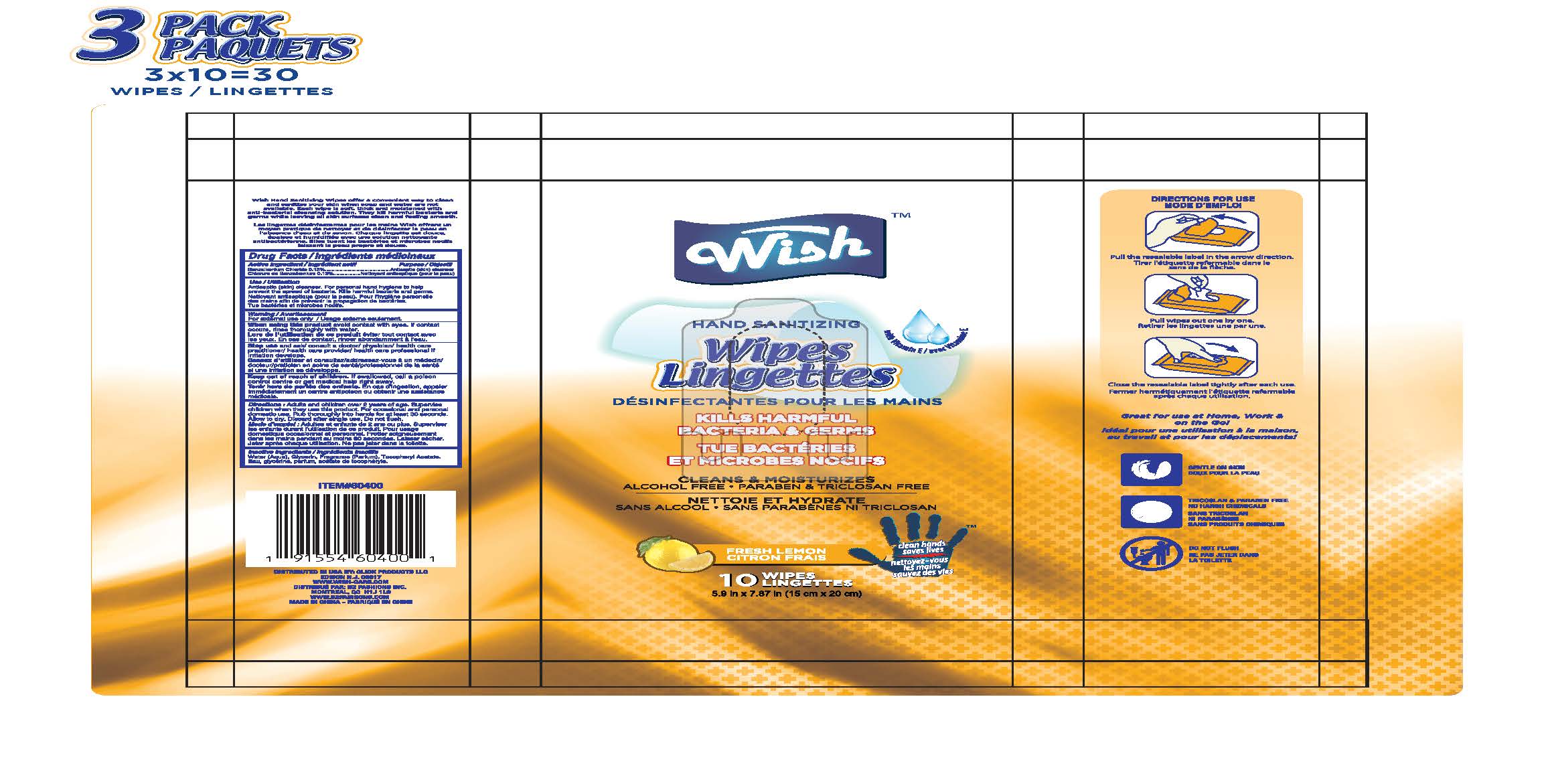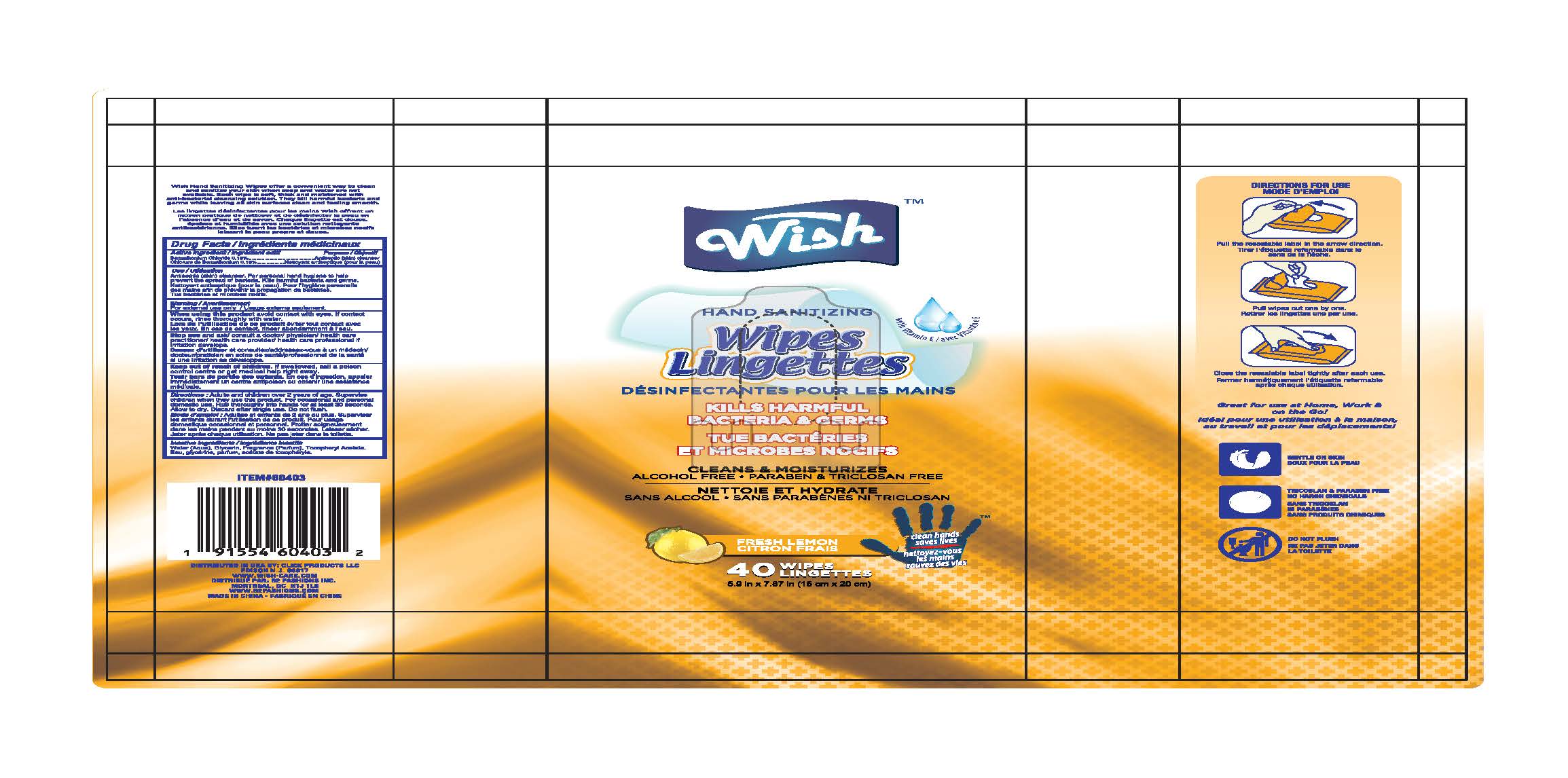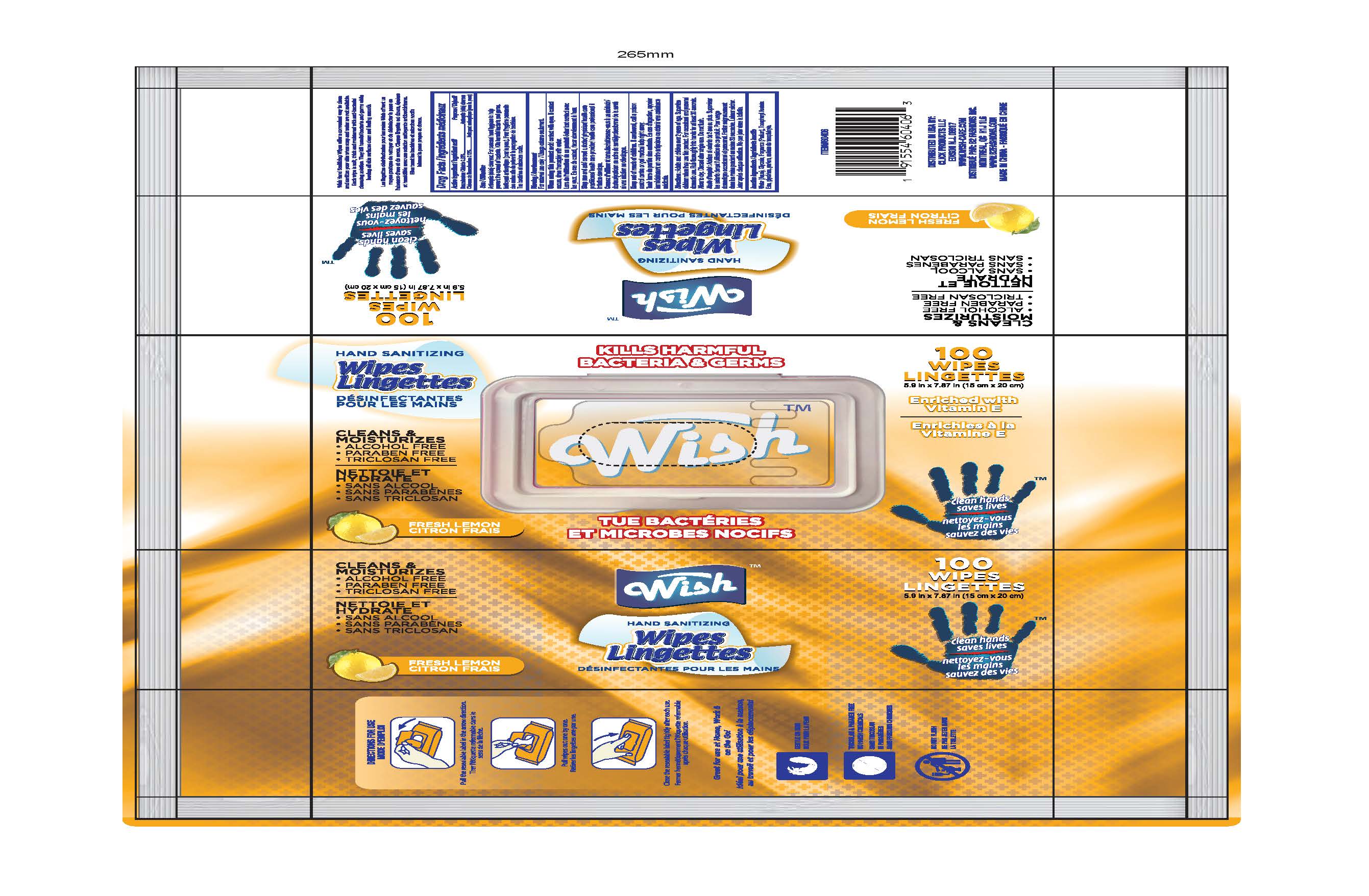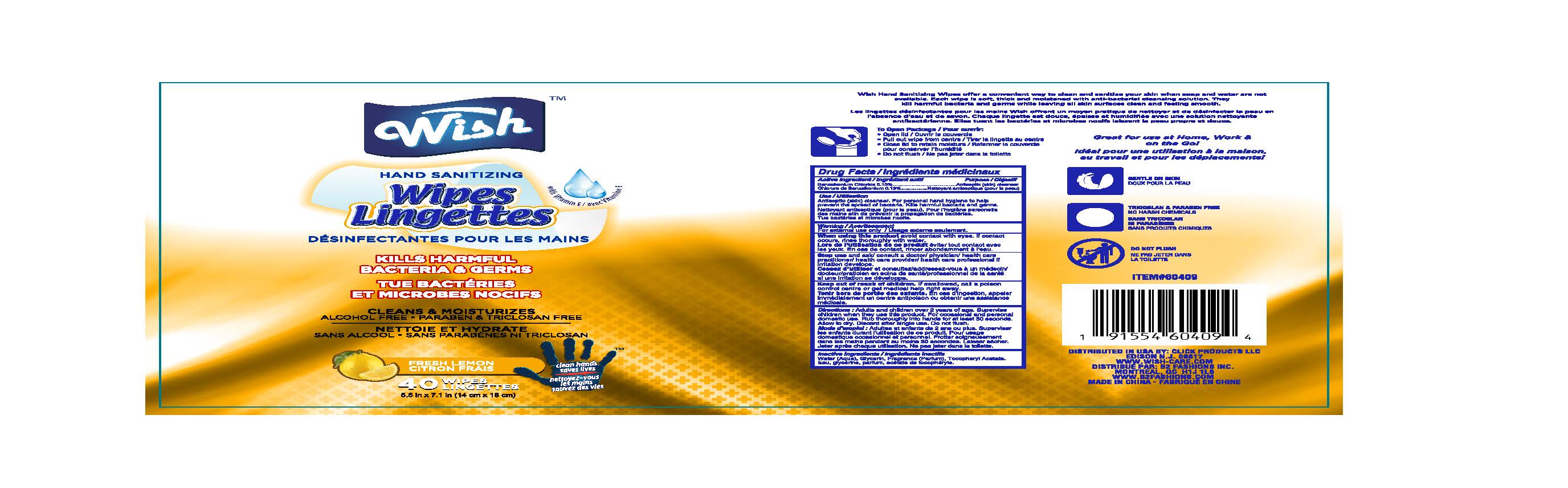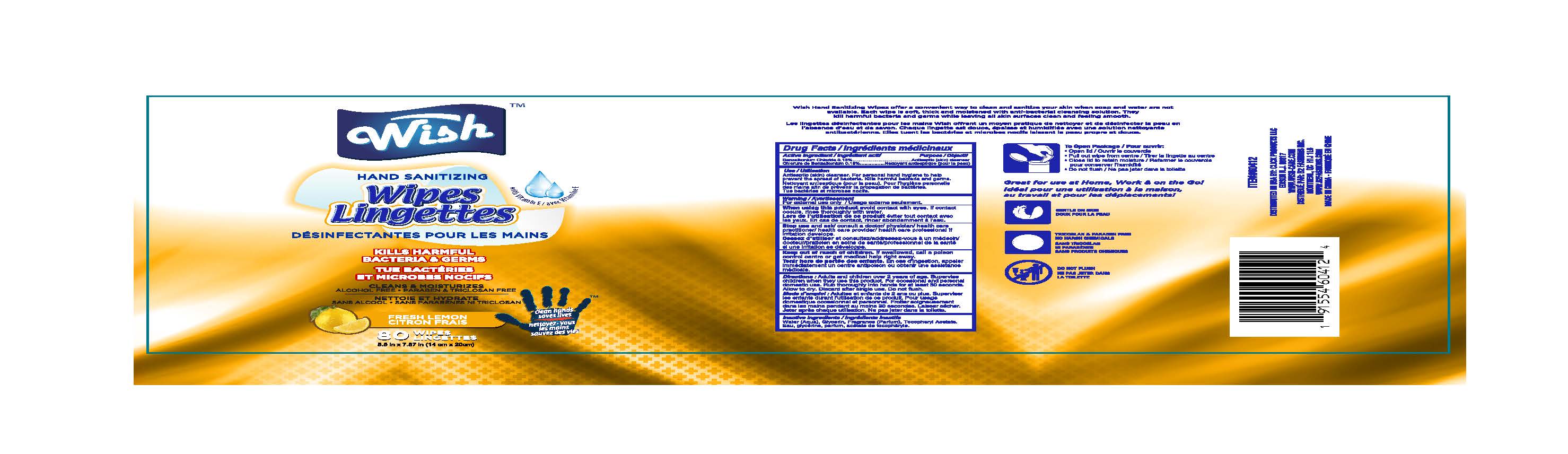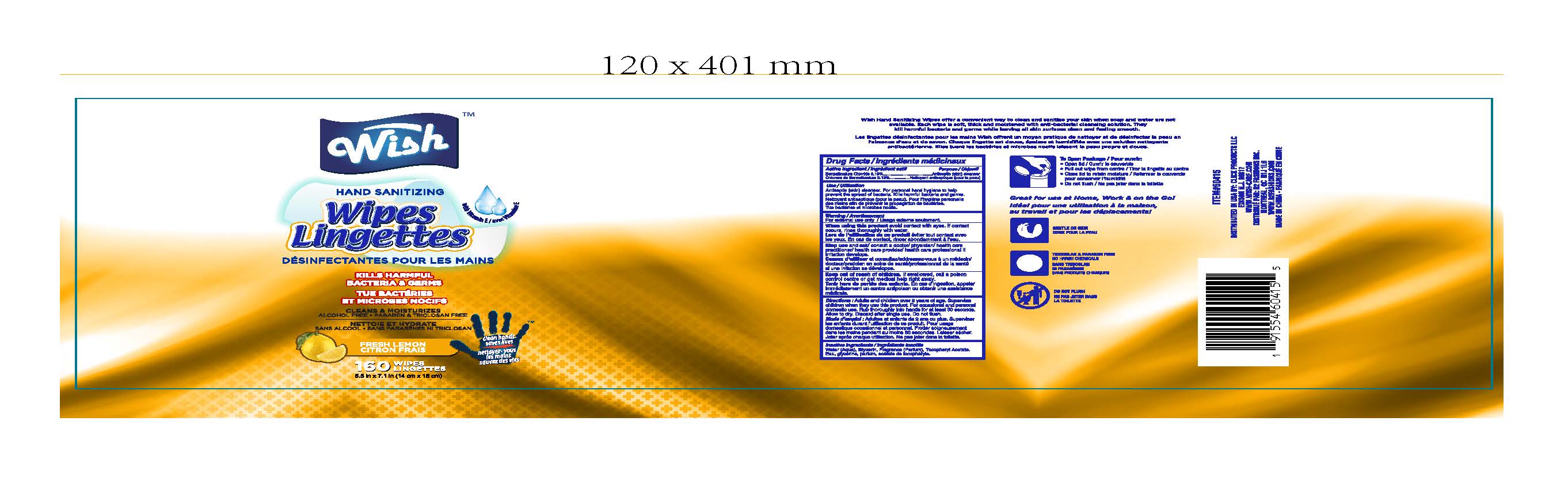 DRUG LABEL: Antiseptic Wipes
NDC: 71611-061 | Form: CLOTH
Manufacturer: Click Products LLC
Category: otc | Type: HUMAN OTC DRUG LABEL
Date: 20201210

ACTIVE INGREDIENTS: BENZALKONIUM CHLORIDE 0.0013 mg/100 mg
INACTIVE INGREDIENTS: GLYCERIN; .ALPHA.-TOCOPHEROL ACETATE; WATER

Wish Hand Sanitizing Wipes

Active ingredients

Benalkonium chloride (0.13%)

Purpose

Antibacterial

Use

decrease bacteria on skin

Warnings

For external use only

Do Not Use

if you are allergic to any of the ingredients

When using this product

donot get into eyes.

if contact occurs, rinse thoroughly with water.

Stop use and ask a doctor if

irritation or rash develops.

and continues for more than 72 hours

Keep out of reach of children.

If swallowed, get medical help or contact a Poison Control Center right away

Directions:

*adults and children 2 years and over

- apply to hands
- allow to dry without wiping

*children under 2 years

- ask a doctor before use

Inactive ingredients

Water (Aqua),
Glycerin,
Fragrance,

Tocopheryl Acetate